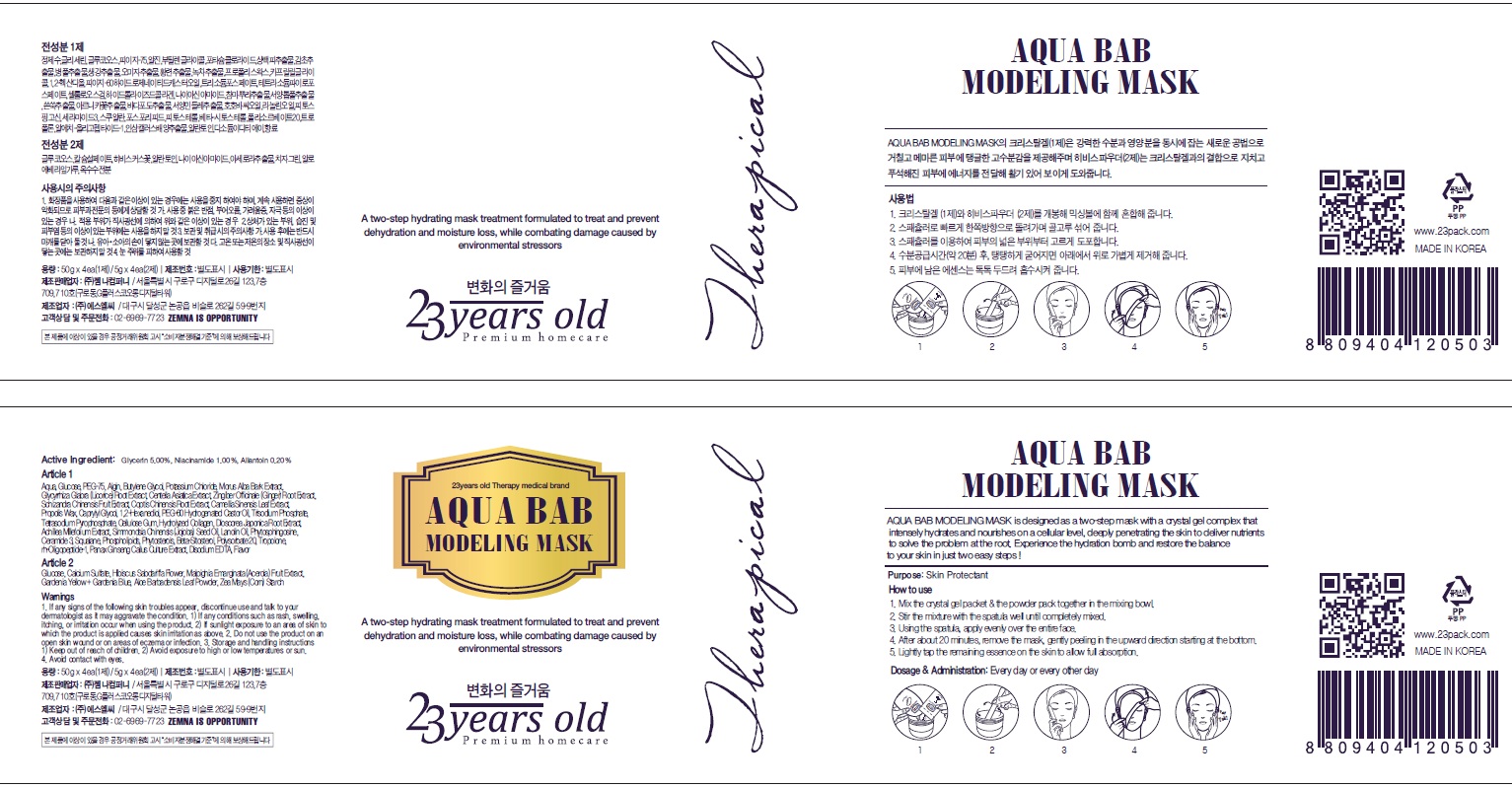 DRUG LABEL: Aqua Bab Modeling Mask
NDC: 70768-030 | Form: GEL
Manufacturer: ZEMNA COMPANY CO., Ltd
Category: otc | Type: HUMAN OTC DRUG LABEL
Date: 20160719

ACTIVE INGREDIENTS: Glycerin 10 g/220 g; Niacinamide 2.2 g/220 g; Allantoin 0.04 g/220 g
INACTIVE INGREDIENTS: WATER

ACTIVE INGREDIENT

Active Ingredient: Glycerin 5.00%, Niacinamide 1.00%, Allantoin 0.20%

INACTIVE INGREDIENT

Inactive Ingredients:

Article 1: Aqua, Glucose, PEG-75, Algin, Butylene Glycol, Potassium Chloride, Morus Alba Bark Extract, Glycyrrhiza Glabra (Licorice) Root Extract, Centella Asiatica Extract, Zingiber Officinale (Ginger) Root Extract, Schizandra Chinensis Fruit Extract, Coptis Chinensis Root Extract, Camellia Sinensis Leaf Extract, Propolis Wax, Caprylyl Glycol, 1,2-Hexanediol, PEG-60 Hydrogenated Castor Oil, Trisodium Phosphate, Tetrasodium Pyrophosphate, Cellulose Gum, Hydrolyzed Collagen, Dioscorea Japonica Root Extract, Achillea Millefolium Extract, Simmondsia Chinensis (Jojoba) Seed Oil, Lanolin Oil, Phytosphingosine, Ceramide 3, Squalane, Phospholipids, Phytosterols, Beta-Sitosterol, Polysorbate 20, Tropolone, rh-Oligopeptide-1, Panax Ginseng Callus Culture Extract, Disodium EDTA, Flavor

Article 2:Glucose, Calcium Sulfate, Hibiscus Sabdariffa Flower, Malpighia Emarginata (Acerola) Fruit Extract, Gardenia Yellow + Gardenia Blue, Aloe Barbadensis Leaf Powder, Zea Mays (Corn) Starch

PURPOSE

Purpose: Skin Protectant

WARNINGS

Warnings: 1. If any signs of the following skin troubles appear, discontinue use and talk to your dermatologist as it may aggravate the condition. 1) If any conditions such as rash, swelling, itching, or irritation occur when using the product. 2) If sunlight exposure to an area of skin to which the product is applied causes skin irritation as above. 2. Do not use the product on an open skin wound or on areas of eczema or infection. 3. Storage and handling instructions 1) Keep out of reach of children. 2) Avoid exposure to high or low temperatures or sun. 4. Avoid contact with eyes.

KEEP OUT OF REACH OF CHILDREN

How to use: 1) Mix the crystal gel packet & the powder pack together in the mixing bowl. 2) Stir the mixture with the spatula well until completely mixed 3) Using the spatula, apply evenly over the entire face. 4) After about 20minutes, remove the mask, gently peeling in the upward direction starting at the bottom. 5) Lightly tap the remaining essence on the skin to allow full absorption

DOSAGE & ADMINISTRATION

Dosage & Administration: Every day or every other day